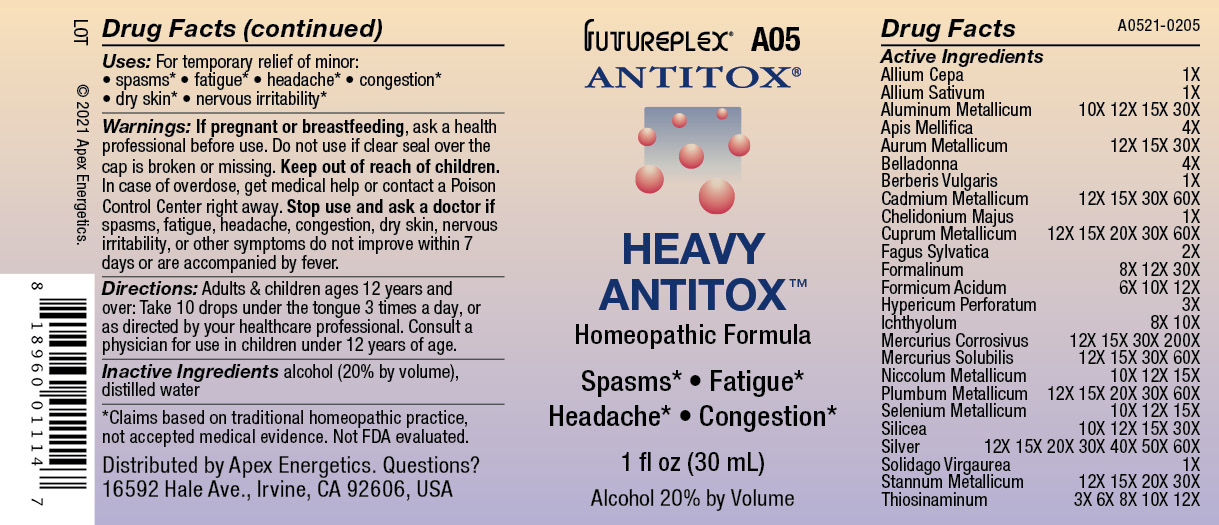 DRUG LABEL: A05
NDC: 63479-0105 | Form: SOLUTION/ DROPS
Manufacturer: Apex Energetics Inc.
Category: homeopathic | Type: HUMAN OTC DRUG LABEL
Date: 20240108

ACTIVE INGREDIENTS: APIS MELLIFERA 4 [hp_X]/1 mL; GOLD 30 [hp_X]/1 mL; HYPERICUM PERFORATUM 3 [hp_X]/1 mL; ICHTHAMMOL 10 [hp_X]/1 mL; MERCURIUS SOLUBILIS 60 [hp_X]/1 mL; LEAD 60 [hp_X]/1 mL; GARLIC 1 [hp_X]/1 mL; ALUMINUM 30 [hp_X]/1 mL; ATROPA BELLADONNA 4 [hp_X]/1 mL; FORMALDEHYDE 30 [hp_X]/1 mL; FORMIC ACID 12 [hp_X]/1 mL; SILVER 60 [hp_X]/1 mL; CHELIDONIUM MAJUS 1 [hp_X]/1 mL; COPPER 60 [hp_X]/1 mL; SILICON DIOXIDE 30 [hp_X]/1 mL; CADMIUM 60 [hp_X]/1 mL; FAGUS SYLVATICA NUT 2 [hp_X]/1 mL; BERBERIS VULGARIS ROOT BARK 1 [hp_X]/1 mL; MERCURIC CHLORIDE 200 [hp_X]/1 mL; SOLIDAGO VIRGAUREA FLOWERING TOP 1 [hp_X]/1 mL; TIN 30 [hp_X]/1 mL; ALLYLTHIOUREA 12 [hp_X]/1 mL; ONION 1 [hp_X]/1 mL; NICKEL 15 [hp_X]/1 mL; SELENIUM 15 [hp_X]/1 mL
INACTIVE INGREDIENTS: WATER; ALCOHOL

A05

Active Ingredients
Allium Cepa | 1X
Allium Sativum | 1X
Aluminium Metallicum | 10X 12X 15X 30X
Apis Mellifica | 4X
Argentum Metallicum | 12X 15X 20X 30X 40X 50X 60X
Aurum Metallicum | 12X 15X 30X
Belladonna | 4X
Berberis Vulgaris | 1X
Cadmium Metallicum | 12X 15X 30X 60X
Chelidonium Majus | 1X
Cuprum Metallicum | 12X 15X 20X 30X 60X
Fagus Sylvatica | 2X
Formalinum | 8X 12X 30X
Formicum Acidum | 6X 10X 12X
Hypericum Perforatum | 3X
Ichthyolum | 8X 10X
Mercurius Corrosivus | 12X 15X 30X 200X
Mercurius Solubilis | 12X 15X 30X 60X
Niccolum Metallicum | 10X 12X 15X
Plumbum Metallicum | 12X 15X 20X 30X 60X
Selenium Metallicum | 10X 12X 15X
Silicea | 10X 12X 15X 30X
Solidago Virgaurea | 1X
Stannum Metallicum | 12X 15X 20X 30X
Thiosinaminum | 3X 6X 8X 10X 12X

INDICATIONS AND USAGE

Uses:

For temporary relief of minor:

spasms*

fatigue*

headache*

congestion*

dry skin*

nervous irritability*

*Claims based on traditional homeopathic practice, not accepted medical evidence. Not FDA evaluated.

Warnings:

PREGNANCY OR BREAST FEEDING

If pregnant or breastfeeding, ask a health professional before use.

Do not use if clear seal over the cap is broken or missing.

Keep out of reach of children. In case of overdose, get medical help or contact a Poison Control Center right away.

Stop use and ask a doctor if spasms, fatigue, headache, congestion, dry skin, nervous irritability, or other symptoms do not improve within 7 days or are accompanied by fever.

Directions:

Adults & children ages 12 years and over: Take 10 drops under the tongue 3 times a day, or as directed by your healthcare professional. Consult a physician for use in children under 12 years of age.

Inactive Ingredients

alcohol (20% by volume), distilled water

Distributed by Apex Energetics. Questions?

16592 Hale Ave., Irvine, CA 92606, USA

PACKAGE LABEL

FUTUREPLEX® A05

ANTITOX®

HEAVY ANTITOX™

Homeopathic Formula

Spasms*

Fatigue*

Headache*

Congestion*

1 fl oz (30 mL)

Alcohol 20% by Volume